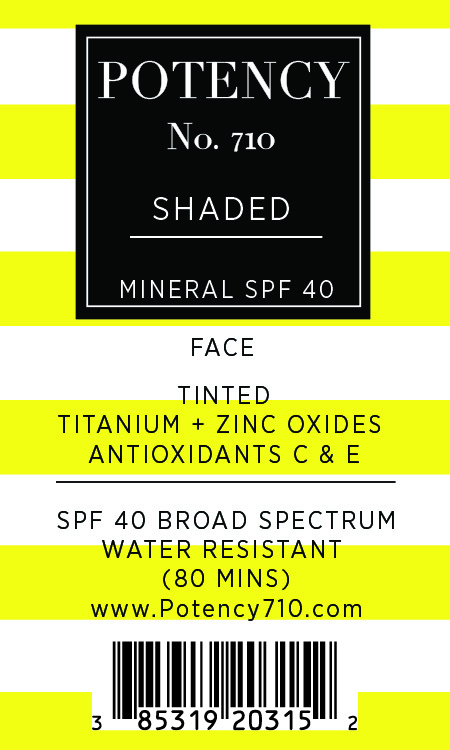 DRUG LABEL: SHADED
NDC: 85319-203 | Form: CREAM
Manufacturer: Potency No. 710 LLC
Category: otc | Type: HUMAN OTC DRUG LABEL
Date: 20251210

ACTIVE INGREDIENTS: TITANIUM DIOXIDE 80 mg/1 g; ZINC OXIDE 38 mg/1 g
INACTIVE INGREDIENTS: ALUMINA; DIMETHICONE; DIMETHICONE CROSSPOLYMER; CI 77491; LAURYL PEG/PPG-18/18 METHICONE; HYDROGEN DIMETHICONE (20 CST); TETRAHEXYLDECYL ASCORBATE; CYCLOHEXASILOXANE; DIMETHICONE/VINYL DIMETHICONE CROSSPOLYMER (SOFT PARTICLE); DIMETHICONOL (2000 CST); CI 77499; CI 77492; PEG-10 DIMETHICONE (600 CST); CYCLOPENTASILOXANE; ALPHA-TOCOPHEROL ACETATE

Active Ingredients:

Titanium Dioxide 8% Zinc Oxide 3.8%

Purpose:

Sunscreen

Warning:

For External Use Only

Warning:

- For External Use Only
- Keep Out of Reach of Children

Warning:

Keep out of reach of children

Directions:

Apply liberally 15 minutes before sun exposure

INACTIVE INGREDIENT

Alumina, Cyclohexasiloxane, Cyclopentasiloxane, Dimethicone, Dimethicone Crosspolymer, Dimethicone/Vinyl Dimethicone Crosspolymer, Dimethiconol, Iron Oxide (CI 77491), Lauryl PEG/PPG-18/18 Methicone, Hydrogen Dimethicone, PEG-10 Dimethicone, Tetrahexyldecyl Ascorbate, Tocopheryl Acetate

OTHER SAFETY INFORMATION

SAMPLE NOT FOR RESALE